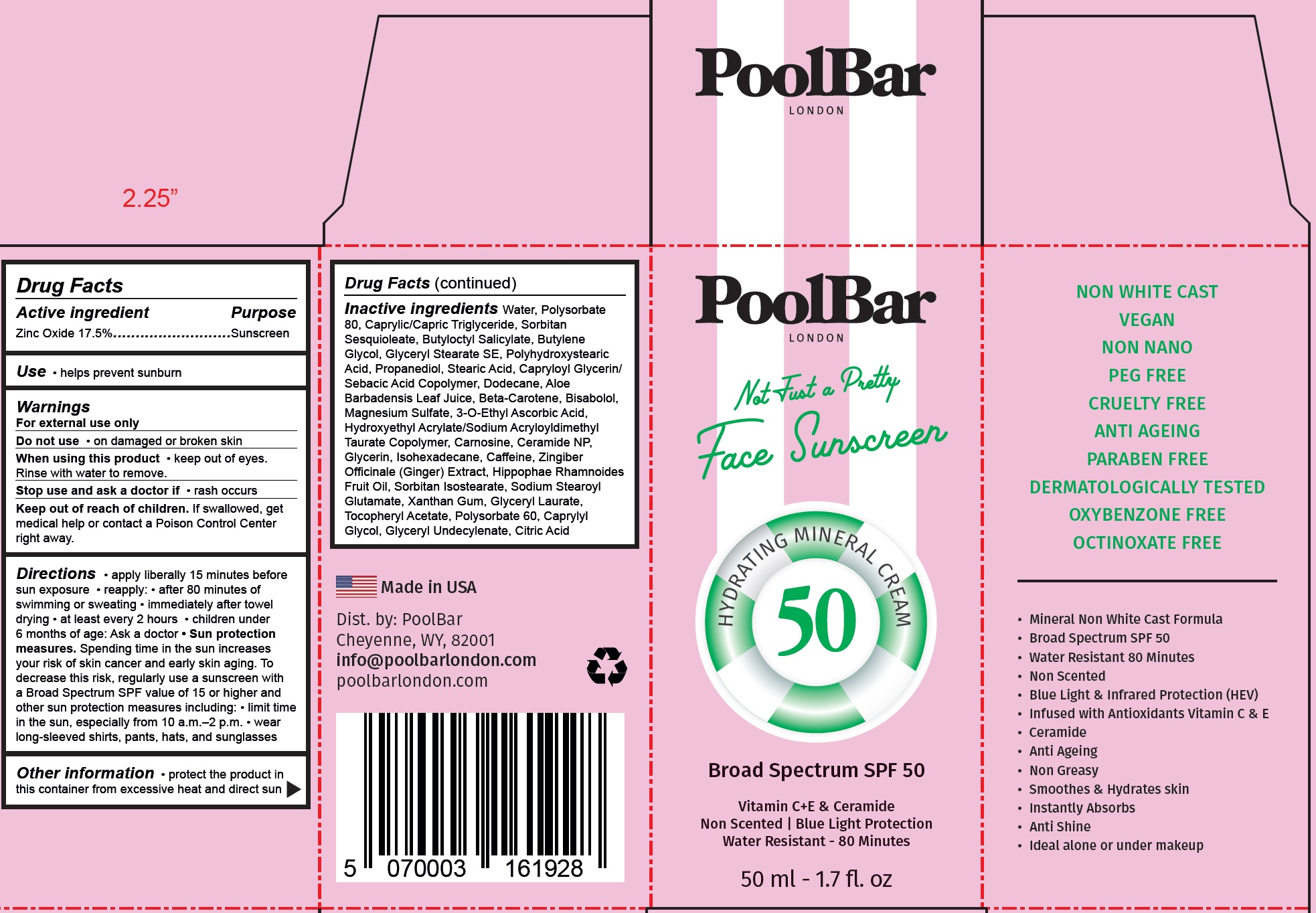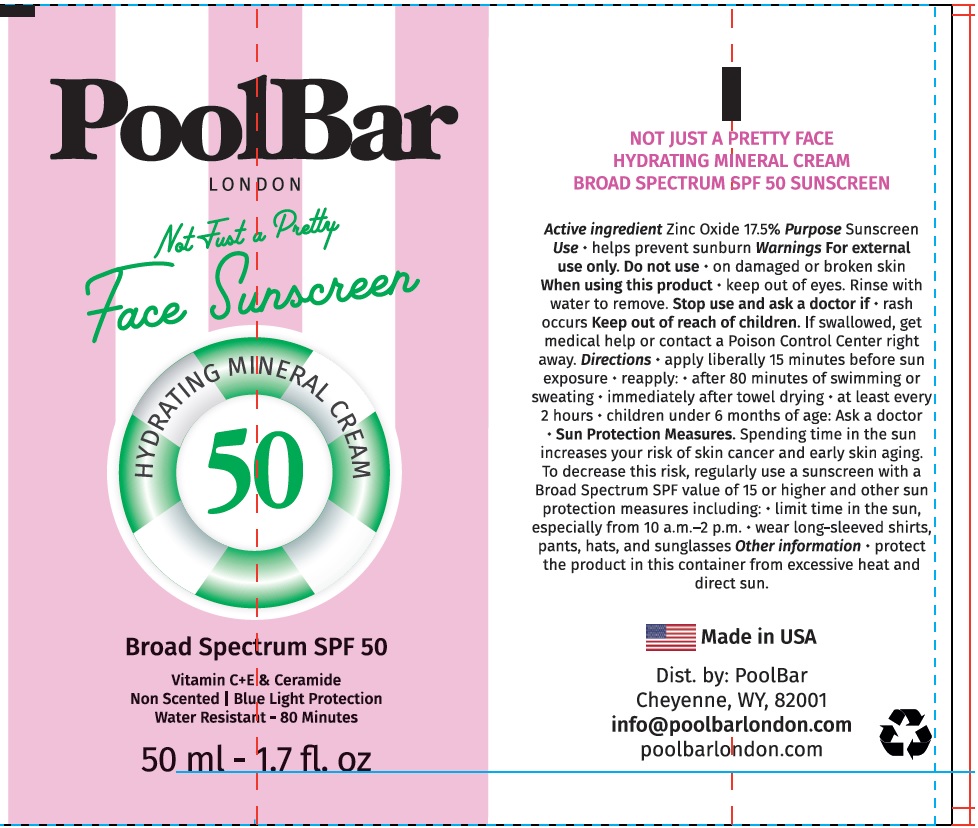 DRUG LABEL: Pool Bar London Not Just a Pretty Face Sunscreen SPF 50
NDC: 84953-565 | Form: CREAM
Manufacturer: POOLBAR
Category: otc | Type: HUMAN OTC DRUG LABEL
Date: 20241119

ACTIVE INGREDIENTS: ZINC OXIDE 175 mg/1 mL
INACTIVE INGREDIENTS: WATER; POLYSORBATE 80; CAPRYLIC/CAPRIC TRIGLYCERIDE; SORBITAN SESQUIOLEATE; BUTYLOCTYL SALICYLATE; BUTYLENE GLYCOL; GLYCERYL STEARATE SE; PROPANEDIOL; STEARIC ACID; DODECANE; ALOE VERA LEAF; BETA-CAROTENE; BISABOLOL; MAGNESIUM SULFATE; 3-O-ETHYL ASCORBIC ACID; CARNOSINE; CERAMIDE NP; GLYCERIN; ISOHEXADECANE; CAFFEINE; HIPPOPHAE RHAMNOIDES FRUIT OIL; SORBITAN ISOSTEARATE; SODIUM STEAROYL GLUTAMATE; XANTHAN GUM; GLYCERYL LAURATE; .ALPHA.-TOCOPHEROL ACETATE; POLYSORBATE 60; CAPRYLYL GLYCOL; CITRIC ACID MONOHYDRATE

Pool Bar London Not Just a Pretty Face Sunscreen SPF 50

Active ingredient

Zinc Oxide 17.5%

Purpose

Sunscreen

Use

- helps prevent sunburn

Warnings

For external use only

Do not use

- on damaged or broken skin

When using this product

- keep out of eyes. Rinse with water to remove.

Stop use and ask a doctor if

- rash occurs

Keep out of reach of children.

If swallowed, get medical help or contact a Poison Control Center right away.

Directions

- apply liberally 15 minutes before sun exposure
- reapply:
- after 80 minutes of swimming or sweating
- immediately after towel drying
- at least every 2 hours
- children under 6 months of age: Ask a doctor
- Sun protection measures.Spending time in the sun increases your risk of skin cancer and early skin aging. To decrease the risk, regularly use a sunscreen with a Broad Spectrum SPF of 15 or higher and other sun protection measures including:limit time in the sun, especially from 10 a.m. - 2 p.m.
- wear long-sleeved shirts, pants, hats, and sunglasses

Other information

- protect the product in this container from excessive heat and direct sun

Inactive ingredients

Water, Polysorbate 80, Caprylic/Capric Triglyceride, Sorbitan Sesquioleate, Butyloctyl Salicylate, Butylene Glycol, Glyceryl Stearate SE, Polyhydroxystearic Acid, Propanediol, Stearic Acid, Capryloyl Glycerin/ Sebacic Acid Copolymer, Dodecane, Aloe Barbadensis Leaf Juice, Beta-Carotene, Bisabolol, Magnesium Sulfate, 3-O-Ethyl Ascorbic Acid, Hydroxyethyl Acrylate/Sodium Acryloyldimethyl Taurate Copolymer, Carnosine, Ceramide NP, Glycerin, Isohexadecane, Caffeine, Zingiber Officinale (Ginger) Extract, Hippophae Rhamnoides Fruit Oil, Sorbitan Isostearate, Sodium Stearoyl Glutamate, Xanthan Gum, Glyceryl Laurate, Tocopheryl Acetate, Polysorbate 60, Caprylyl Glycol, Glyceryl Undecylenate, Citric Acid